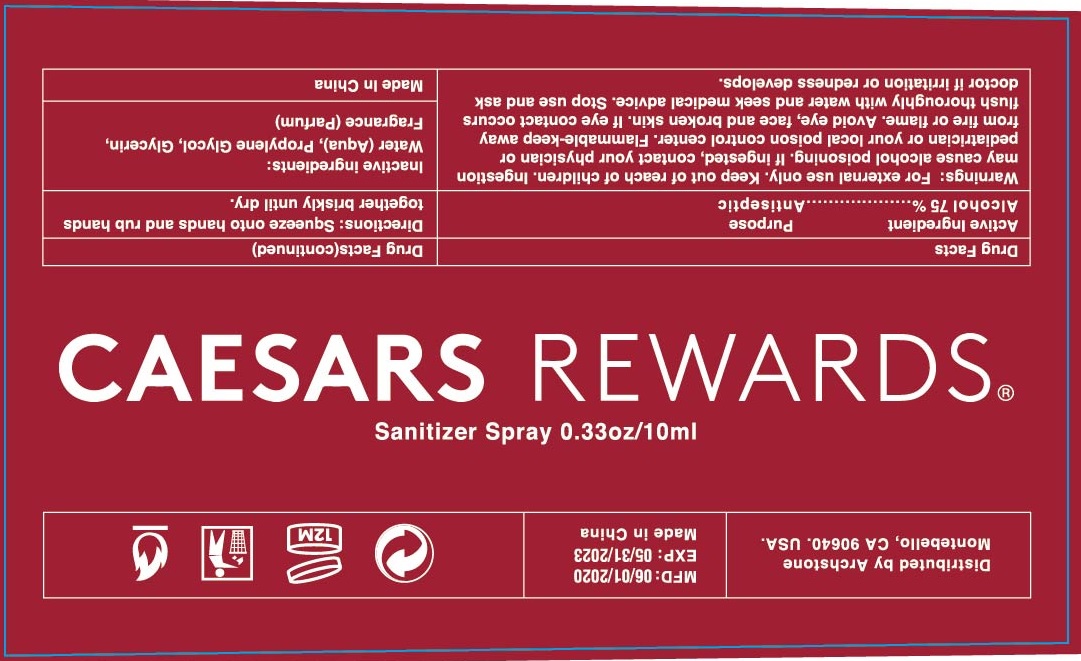 DRUG LABEL: Caesars Rewards Sanitizer
NDC: 75531-003 | Form: SPRAY
Manufacturer: Zhejiang Ounuo Cosmetics Co., Ltd.
Category: otc | Type: HUMAN OTC DRUG LABEL
Date: 20200604

ACTIVE INGREDIENTS: alcohol 75 mL/100 mL
INACTIVE INGREDIENTS: WATER; PROPYLENE GLYCOL; GLYCERIN

Drug facts

Active ingredient - Alcohol 75% (w/w)

Purpose - antiseptic

KEEP OUT OF REACH OF CHILDREN

If swallowed, get medical help or contact a Poison Control Center right away.

INDICATIONS AND USAGE

avoid eye, face and broken skin.

WARNINGS

For external use only
Flammable. Keep away from fire or flame.

When using this products, avoid eye, face and broken skin, if eye contact occurs, flush thoroughly with water and seek medical advise.

Ingestion may cause alcohol poisoning. If ingested, contact your physician or pediatrician or your local poison control center.

Stop using and ask a doctor, if irritation or redness develops.

DOSAGE AND ADMINISTRATION

- Squeeze onto hands and rub hands together briskly until dry.

INACTIVE INGREDIENT

Water (aqua), propylene glycol, Glycerin, Aloe Barbadensis Leaf Extract, Fragrance (parfum).